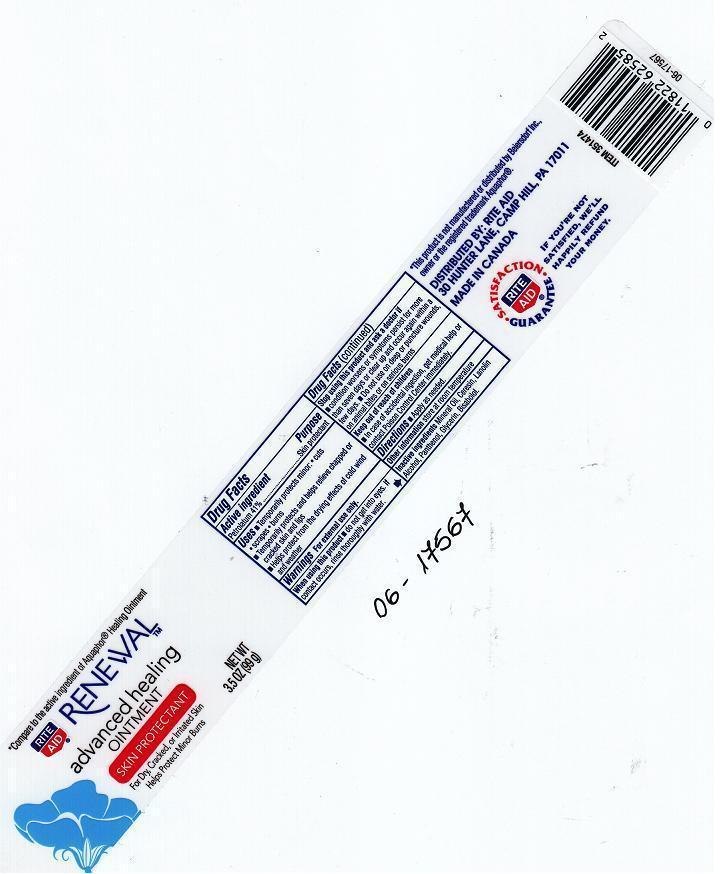 DRUG LABEL: RITE AID RENEWAL
NDC: 11822-3303 | Form: JELLY
Manufacturer: RITE AID CORPORATION
Category: otc | Type: HUMAN OTC DRUG LABEL
Date: 20121030

ACTIVE INGREDIENTS: PETROLATUM 410 mg/1 g
INACTIVE INGREDIENTS: MINERAL OIL; CERESIN; LANOLIN ALCOHOLS; PANTHENOL; GLYCERIN; LEVOMENOL

DRUG FACTS

ACTIVE INGREDIENT

PETROLATUM 41%

PURPOSE

SKIN PROTECTANT

USES

TEMPORARILY PROTECTS MINOR CUTS, SCRAPES, BURNS. TEMPORARILY PROTECTS AND HELPS RELIEVE CHAPPED OR CRACKED SKIN AND LIPS. HELPS PROTECT FROM THE DRYING EFFECTS OF COLD WIND AND WEATHER.

WARNINGS

FOR EXTERNAL USE ONLY.

WHEN USING THIS PRODUCT

DO NOT GET INTO EYES. IF CONTACT OCCURS, RINSE THOROUGHLY WITH WATER.

STOP USING THIS PRODUCT AND ASK A DOCTOR IF

CONDITION WORSENS OR SYMPTOMS PERSIST FOR MORE THAN SEVEN DAYS OR CLEAR UP AND OCCUR AGAIN WITHIN A FEW DAYS. DO NOT USE ON DEEP OR PUNCTURE WOUNDS, ON ANIMAL BITES, OR ON SERIOUS BURNS.

KEEP OUT OF REACH OF CHILDREN

IN CASE OF ACCIDENTAL INGESTION, GET MEDICAL HELP OR CONTACT A POISON CONTROL CENTER IMMEDIATELY.

DIRECTIONS

APPLY AS NEEDED.

OTHER INFORMATION

STORE AT ROOM TEMPERATURE.

INACTIVE INGREDIENTS

MINERAL OIL, CERESIN, LANOLIN ALCOHOL, PANTHENOL, GLYCERIN, BISABOLOL.